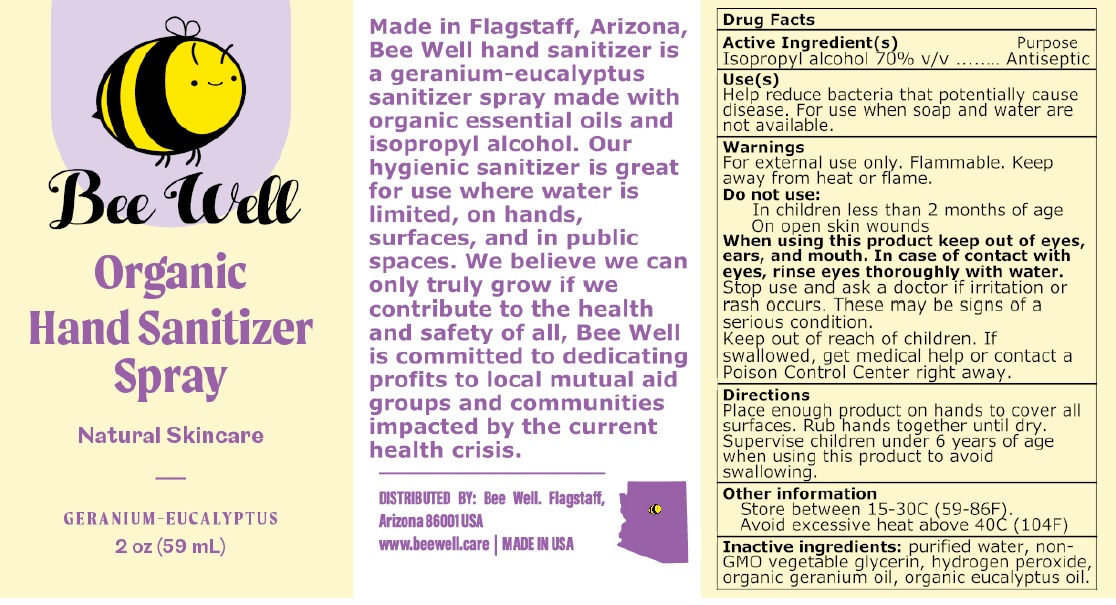 DRUG LABEL: Bee Well
NDC: 80655-420 | Form: SPRAY
Manufacturer: Bee Well LLC
Category: otc | Type: HUMAN OTC DRUG LABEL
Date: 20200915

ACTIVE INGREDIENTS: ISOPROPYL ALCOHOL 70 mL/100 mL
INACTIVE INGREDIENTS: WATER; GLYCERIN; HYDROGEN PEROXIDE; GERANIUM OIL, ALGERIAN TYPE; EUCALYPTUS OIL

Bee Well Organic Hand Sanitizer Spray

Active Ingredient(s)

Isopropyl alcohol 70% v/v

Purpose

Antiseptic

Use(s)

Help reduce bacteria that potentially cause disease. For use when soap and water are not available.

Warnings

For external use only. Flammable. Keep away from heat or flame.

Do not use:

In children less than 2 months of age

On open skin wounds

When using this product keep out of eyes, ears, and mouth. In case of contact with eyes, rinse eyes thoroughly with water.

Stop use and ask a doctor if irritation or rash occurs. These may be signs of a serious condition.

Keep out of reach of children. If swallowed, get medical help or contact a Poison Control Center right away.

Directions

Place enough product on hands to cover all surfaces. Rub hands together until dry. Supervise children under 6 years of age when using this product to avoid swallowing.

Other information

Store between 15-30C (59-86F).

Avoid excessive heat above 40C (104F)

INACTIVE INGREDIENT

Inactive ingredients: purified water, non-GMO vegetable glycerin, hydrogen peroxide, organic geranium oil, organic eucalyptus oil.

Natural Skincare

GERANIUM-EUCALYPTUS

Made in Flagstaff, Arizona, Bee Well hand sanitizer is a geranium-eucalyptus sanitizer spray made with organic essential oils and isopropyl alcohol. Our hygienic sanitizer is great for use where water is limited, on hands, surfaces, and in public spaces. We believe we can only truly grow if we contribute to the health and safety of all, Bee Well is committed to dedicating profits to local mutual aid groups and communities impacted by the current health crisis.

DISTRIBUTED BY: Bee Well. Flagstaff,

Arizona 86001 USA

www.beewell.care | MADE IN USA